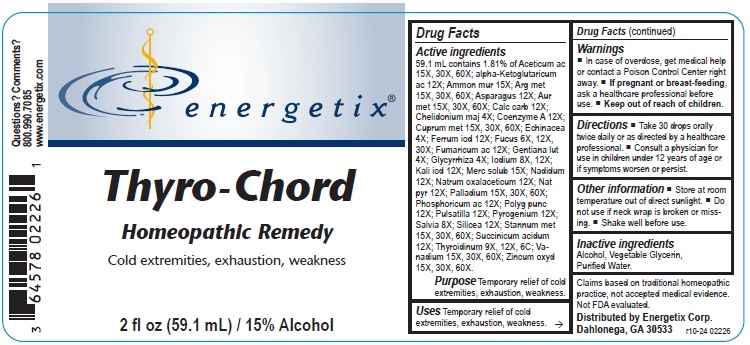 DRUG LABEL: Thyro-Chord
NDC: 64578-0076 | Form: LIQUID
Manufacturer: Energetix Corporation
Category: homeopathic | Type: HUMAN OTC DRUG LABEL
Date: 20250711

ACTIVE INGREDIENTS: ACETIC ACID 15 [hp_X]/59.1 mL; .ALPHA.-KETOGLUTARIC ACID 12 [hp_X]/59.1 mL; AMMONIUM CHLORIDE 15 [hp_X]/59.1 mL; SILVER 15 [hp_X]/59.1 mL; ASPARAGUS 12 [hp_X]/59.1 mL; GOLD 15 [hp_X]/59.1 mL; OYSTER SHELL CALCIUM CARBONATE, CRUDE 12 [hp_X]/59.1 mL; CHELIDONIUM MAJUS 4 [hp_X]/59.1 mL; COENZYME A 12 [hp_X]/59.1 mL; COPPER 15 [hp_X]/59.1 mL; ECHINACEA ANGUSTIFOLIA 4 [hp_X]/59.1 mL; FERROUS IODIDE 12 [hp_X]/59.1 mL; FUCUS VESICULOSUS 6 [hp_X]/59.1 mL; FUMARIC ACID 12 [hp_X]/59.1 mL; GENTIANA LUTEA ROOT 4 [hp_X]/59.1 mL; GLYCYRRHIZA GLABRA 4 [hp_X]/59.1 mL; IODINE 8 [hp_X]/59.1 mL; POTASSIUM IODIDE 12 [hp_X]/59.1 mL; MERCURIUS SOLUBILIS 15 [hp_X]/59.1 mL; NADIDE 12 [hp_X]/59.1 mL; SODIUM DIETHYL OXALACETATE 12 [hp_X]/59.1 mL; SODIUM PYRUVATE 12 [hp_X]/59.1 mL; PALLADIUM 15 [hp_X]/59.1 mL; PHOSPHORIC ACID 12 [hp_X]/59.1 mL; PERSICARIA PUNCTATA 12 [hp_X]/59.1 mL; PULSATILLA VULGARIS 12 [hp_X]/59.1 mL; RANCID BEEF 12 [hp_X]/59.1 mL; SAGE 8 [hp_X]/59.1 mL; SILICON DIOXIDE 12 [hp_X]/59.1 mL; TIN 15 [hp_X]/59.1 mL; SUCCINIC ACID 12 [hp_X]/59.1 mL; THYROID, UNSPECIFIED 9 [hp_X]/59.1 mL; VANADIUM 15 [hp_X]/59.1 mL; ZINC OXIDE 15 [hp_X]/59.1 mL
INACTIVE INGREDIENTS: WATER; GLYCERIN; ALCOHOL

Thyro-Chord

ACTIVE INGREDIENT

Active ingredients59.1 mL contains 1.81% of Aceticum ac 15X, 30X, 60X; alpha-Ketoglutaricum ac 12X; Ammon mur 15X; Arg met 15X, 30X, 60X; Asparagus 12X; Aur met 15X, 30X, 60X; Calc carb 12X; Chelidonium maj 4X; Coenzyme A 12X; Cuprum met 15X, 30X, 60X; Echinacea 4X; Ferrum iod 12X; Fucus 6X, 12X, 30X; Fumaricum ac 12X; Gentiana lut 4X; Glycyrrhiza 4X; Iodium 8X, 12X; Kali iod 12X; Merc solub 15X; Nadidum 12X; Natrum oxalaceticum 12X; Nat pyr 12X; Palladium 15X, 30X, 60X; Phosphoricum ac 12X; Polyg punc 12X; Pulsatilla 12X; Pyrogenium 12X; Salvia 8X; Silicea 12X; Stannum met 15X, 30X, 60X; Succinicum acidum 12X; Thyroidinum 9X, 12X, 6C; Vanadium 15X, 30X, 60X; Zincum oxyd 15X, 30X, 60X.

Claims based on traditional homeopathic practice, not accepted medical evidence. Not FDA evaluated.

Uses

Temporary relief of cold extremities, exhaustion, weakness.

Warnings

- In case of overdose, get medical help or contact a Poison Control Center right away.
- If pregnant or breast-feeding, ask a healthcare professional before use.

- Keep out of reach of children.

Directions

- Take 30 drops orally twice daily or as directed by a healthcare professional.
- Consult a physician for use in children under 12 years of age or if symptoms worsen or persist.

Other information

- Store at room temperature out of direct sunlight.
- Do not use if neck wrap is broken or missing.
- Shake well before use.

Inactive ingredients

Alcohol, Vegetable Glycerin, Purified Water.

QUESTIONS

Distributed by Energetix Corp.

Dahlonega, GA 30533

Questions? 800.990.7085

www.energetix.com

PACKAGE LABEL

energetix

Thyro-Chord

Homeopathic Remedy

Cold extremities, exhaustion, weakness

2 fl oz (59.1 mL) / 15% Alcohol

PURPOSE

PurposeCold extremities, exhaustion, weakness